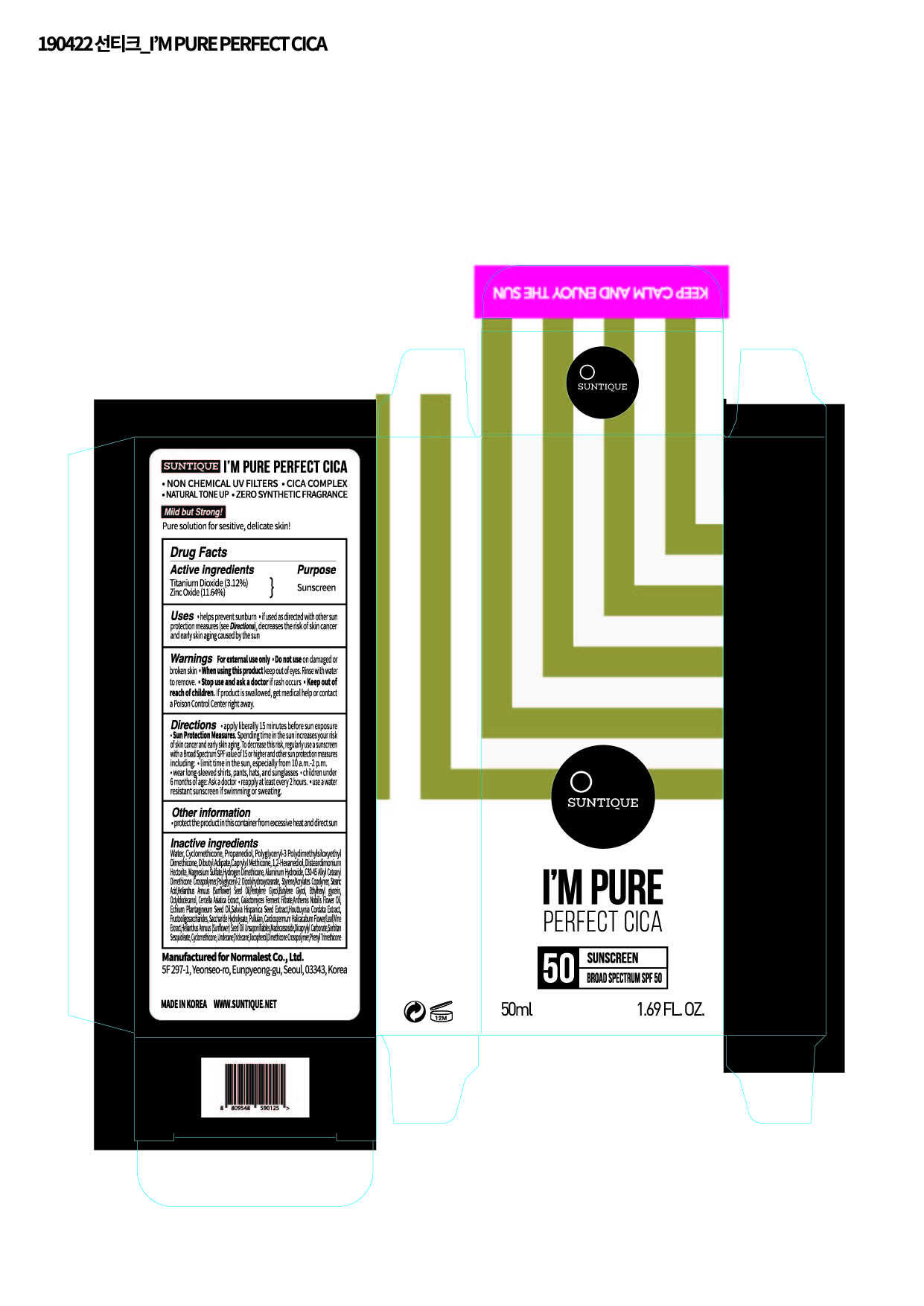 DRUG LABEL: IM PURE PERFECT CICA
NDC: 72284-0008 | Form: LOTION
Manufacturer: Normalest Co., Ltd.
Category: otc | Type: HUMAN OTC DRUG LABEL
Date: 20190423

ACTIVE INGREDIENTS: ZINC OXIDE 5.82 g/50 mL; TITANIUM DIOXIDE 1.56 g/50 mL
INACTIVE INGREDIENTS: DICAPRYLYL CARBONATE; TOCOPHEROL; DISTEARDIMONIUM HECTORITE; POLYGLYCERYL-2 DIPOLYHYDROXYSTEARATE; ECHIUM PLANTAGINEUM SEED OIL; SALVIA HISPANICA SEED; TRIDECANE; MADECASSOSIDE; PROPANEDIOL; DIBUTYL ADIPATE; CAPRYLYL TRISILOXANE; ALUMINUM HYDROXIDE; SORBITAN SESQUIOLEATE; CYCLOMETHICONE; UNDECANE; WATER; 1,2-HEXANEDIOL; MAGNESIUM SULFATE, UNSPECIFIED; PHENYL TRIMETHICONE; STYRENE/ACRYLAMIDE COPOLYMER (MW 500000); STEARIC ACID; SUNFLOWER OIL; PENTYLENE GLYCOL; BUTYLENE GLYCOL; ETHYLHEXYLGLYCERIN; OCTYLDODECANOL; CHAMAEMELUM NOBILE FLOWER OIL; HOUTTUYNIA CORDATA FLOWERING TOP; INVERT SUGAR; PULLULAN; CARDIOSPERMUM HALICACABUM FLOWERING TOP

PACKAGE LABEL

Active Ingredients

Zinc Oxide, Titanium Dioxide

Inactive Ingredients

Water, Cyclopentasiloxane, Propanediol, Polyglyceryl-3 Polydimethylsiloxyethyl Dimethicone, Dibutyl Adipate, Caprylyl Methicone, 1,2-Hexanediol, Disteardimonium Hectorite, Magnesium Sulfate, Hydrogen Dimethicone, Aluminum Hydroxide, C30-45 Alkyl Cetearyl Dimethicone Crosspolymer, Polyglyceryl-2 Dipolyhydroxystearate, Styrene/Acrylates Copolymer, Stearic Acid, Helianthus Annuus (Sunflower) Seed Oil, Pentylene Glycol, Butylene Glycol, Ethylhexylglycerin, Octyldodecanol, Centella Asiatica Extract, Galactomyces Ferment Filtrate, Anthemis Nobilis Flower Oil, Echium Plantagineum Seed Oil, Salvia Hispanica Seed Extract, Houttuynia Cordata Extract, Fructooligosaccharides, Saccharide Hydrolysate, Pullulan, Cardiospermum Halicacabum Flower/Leaf/Vine Extract, Helianthus Annuus (Sunflower) Seed Oil Unsaponifiables, Madecassoside, Dicaprylyl Carbonate, Sorbitan Sesquioleate, Cyclomethicone, Undecane, Tridecane, Tocopherol, Dimethicone Crosspolymer, Phenyl Trimethicone